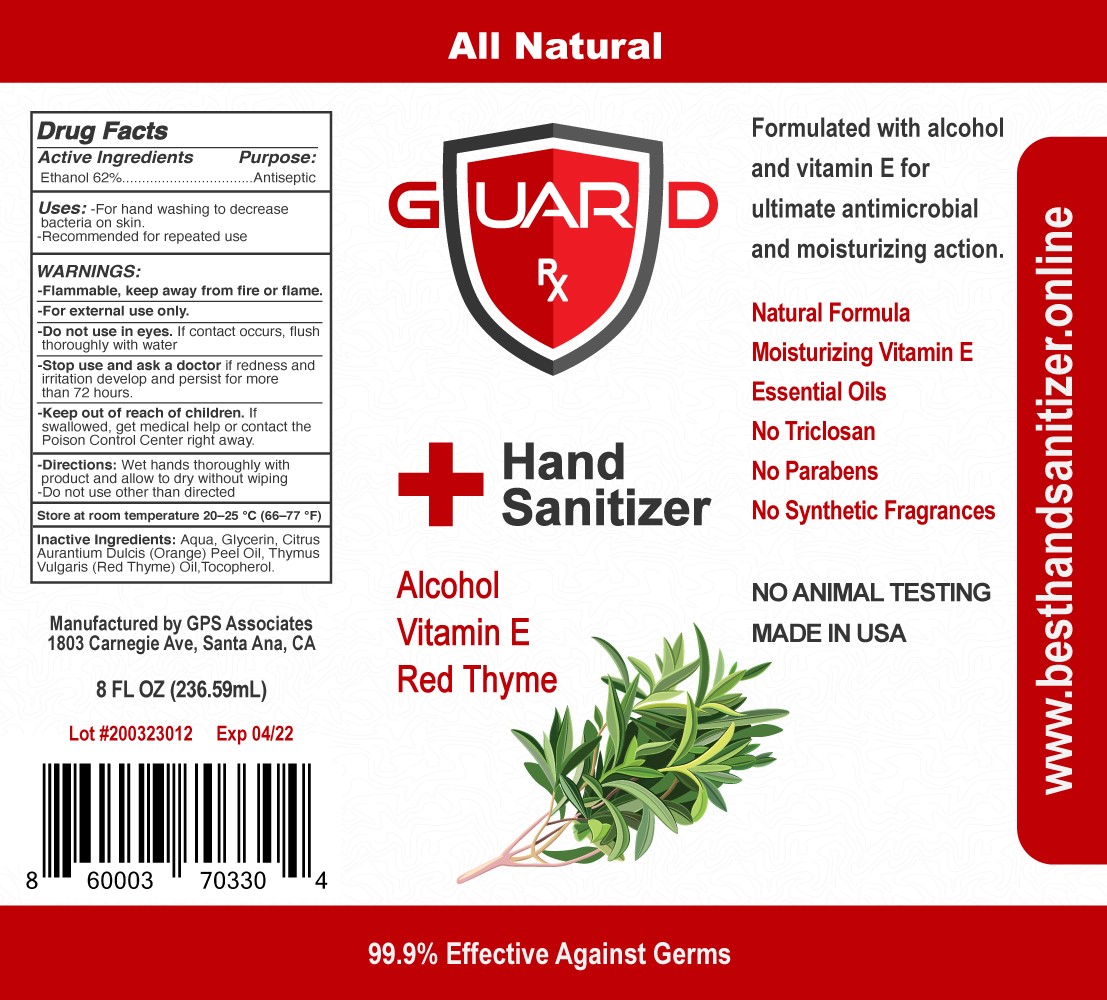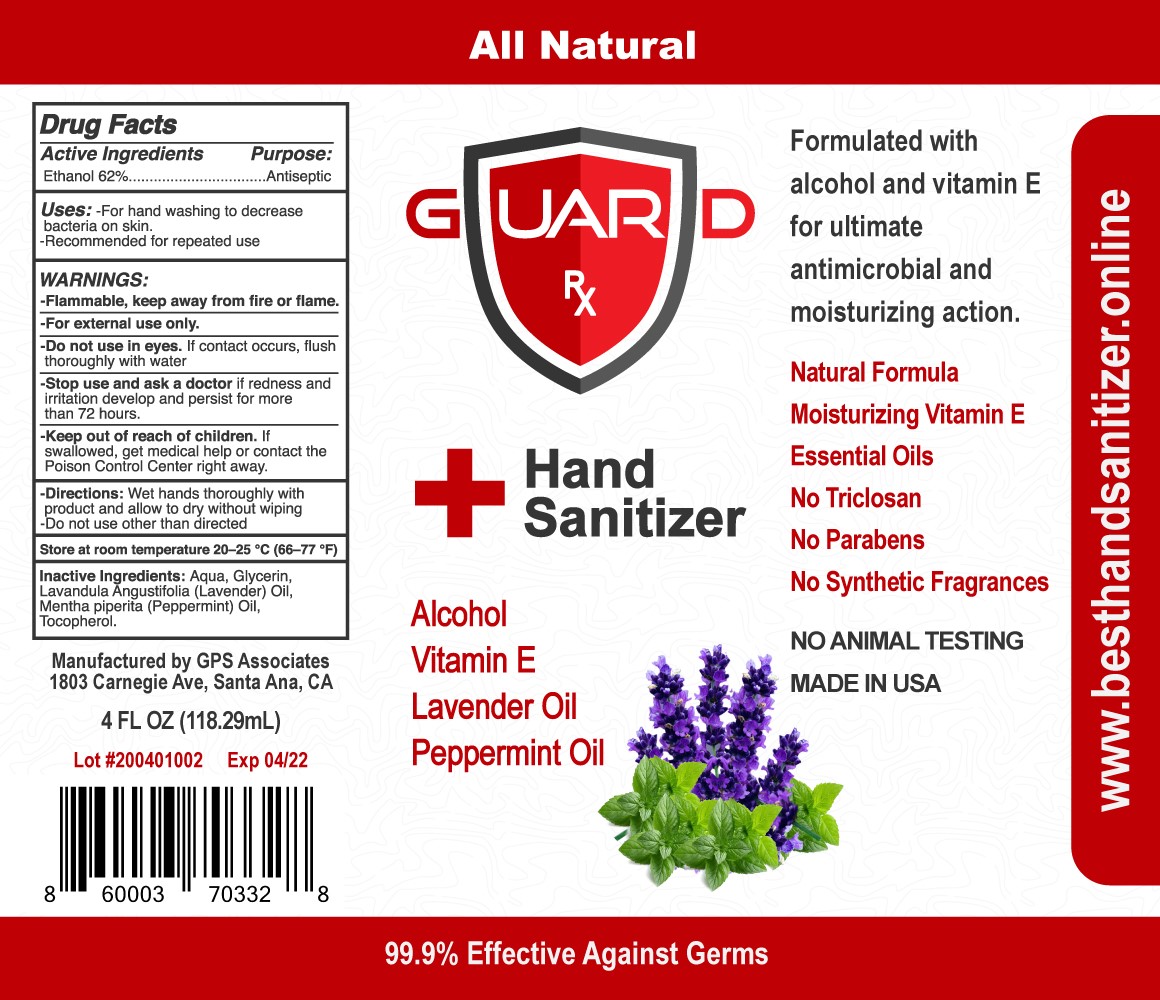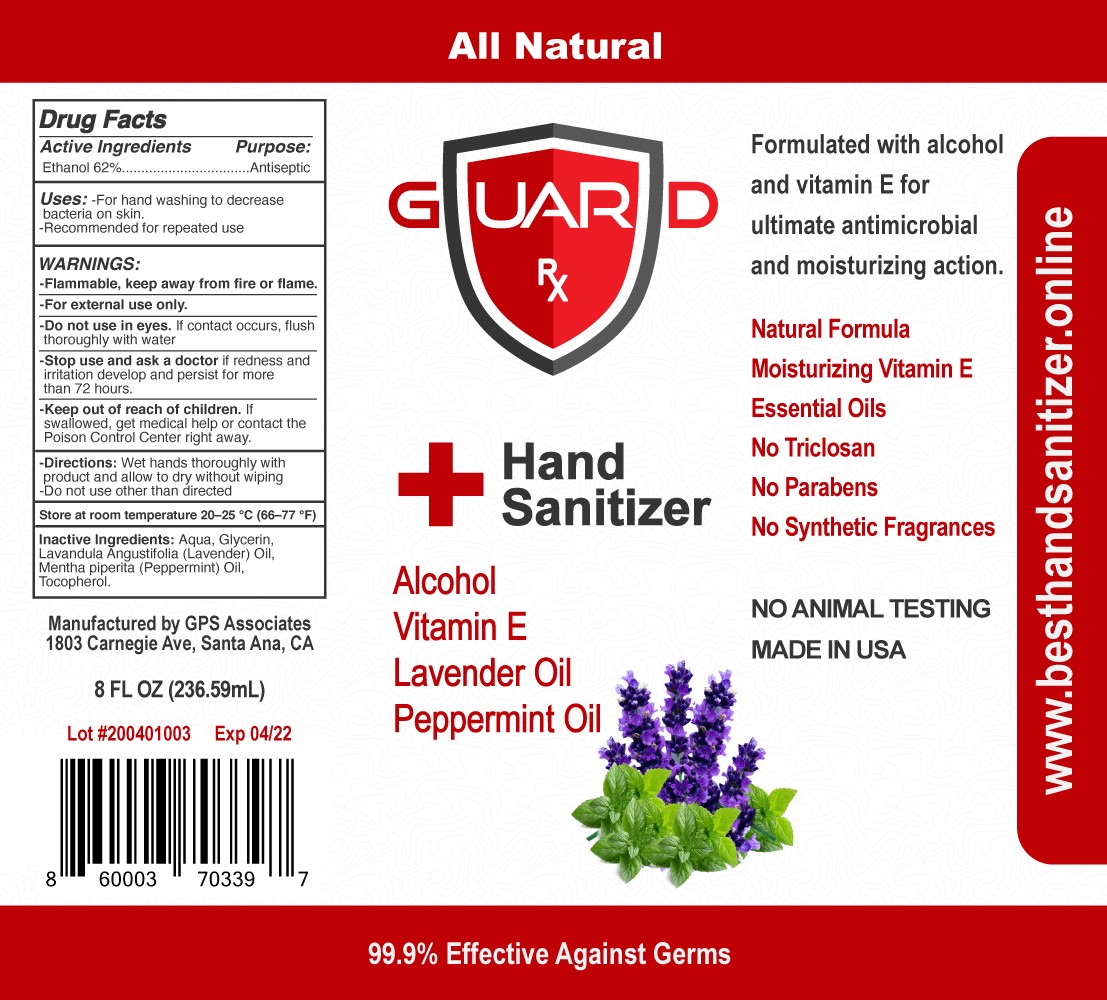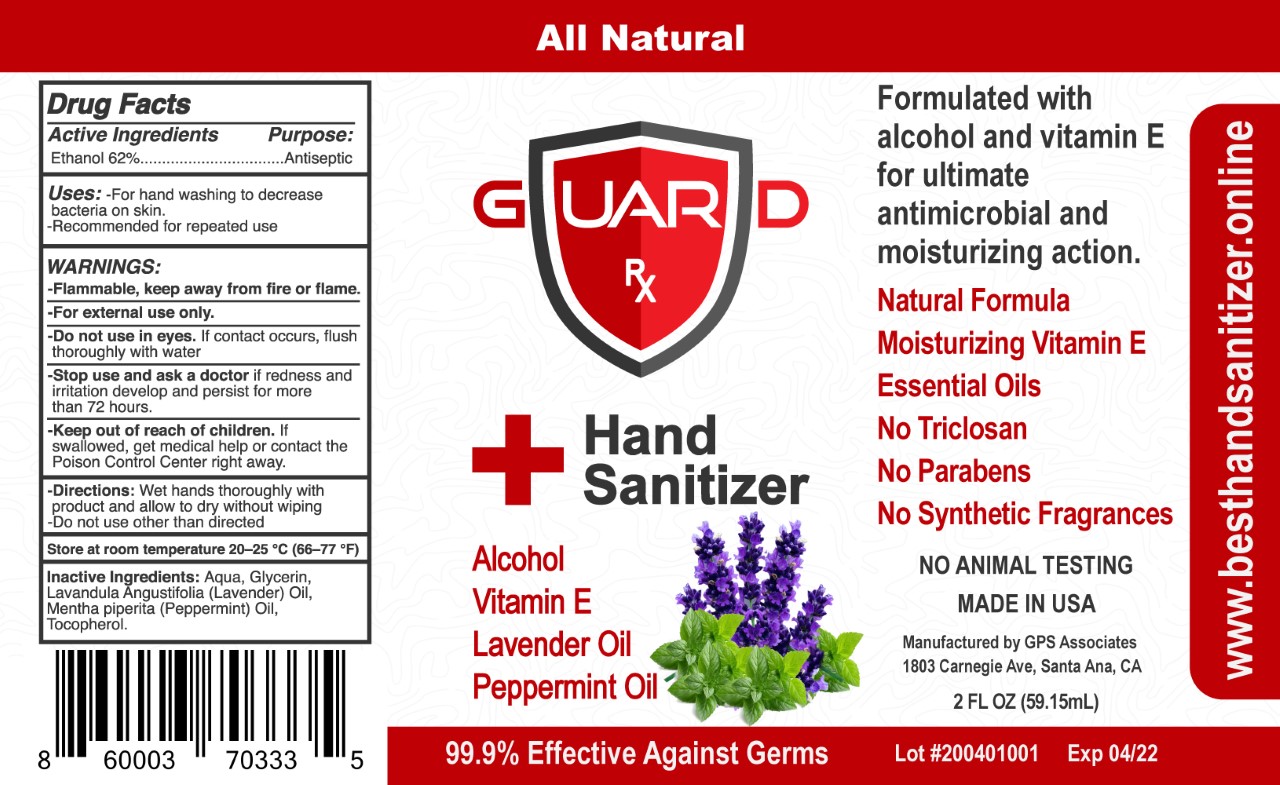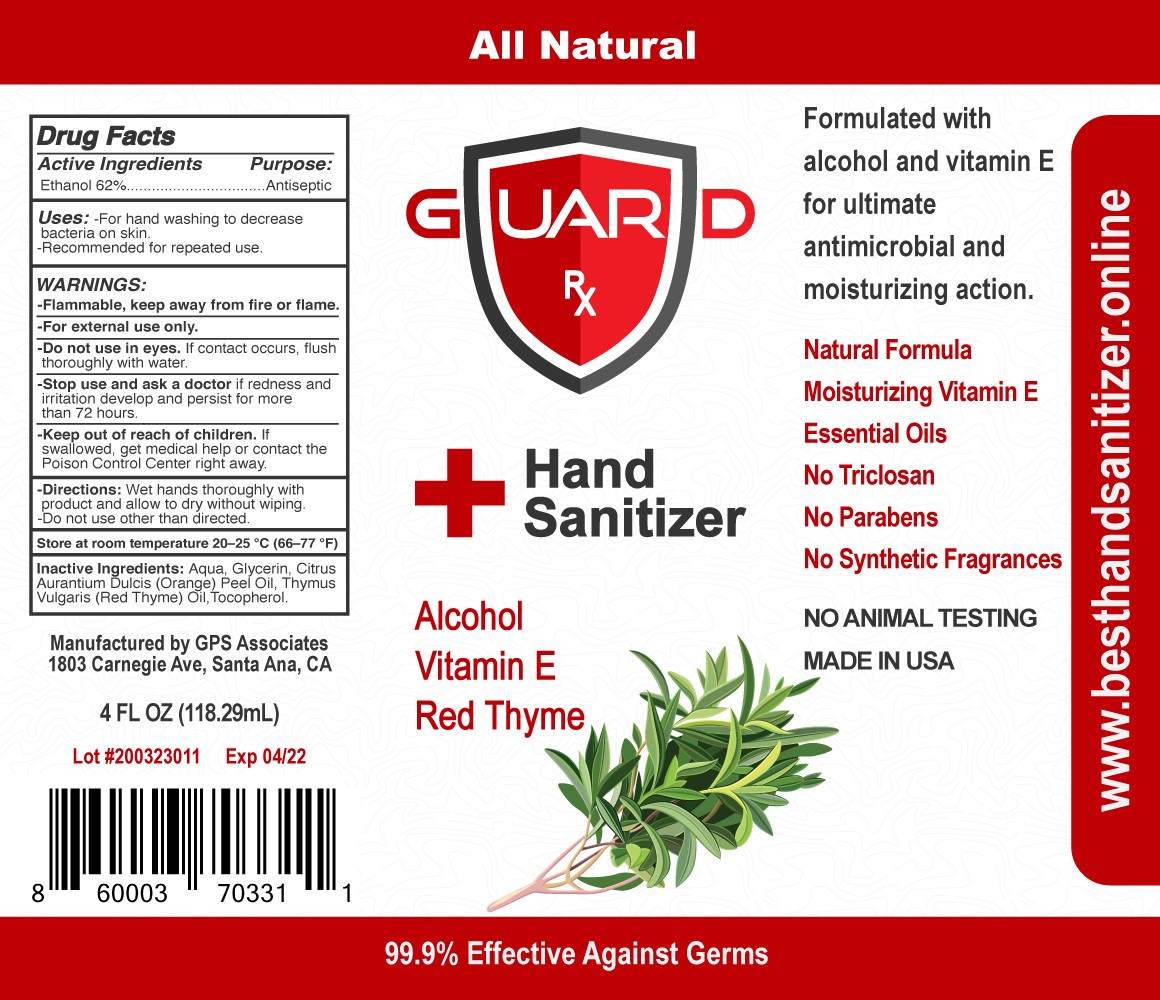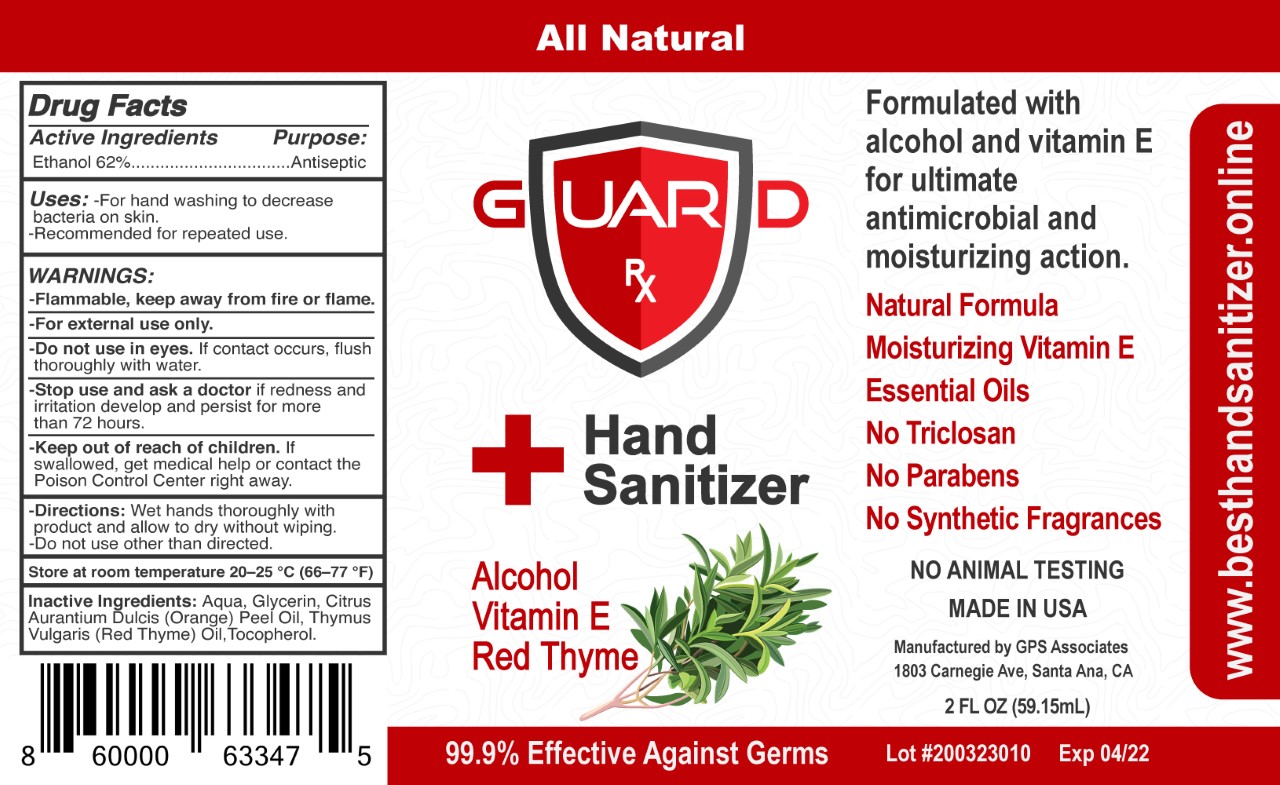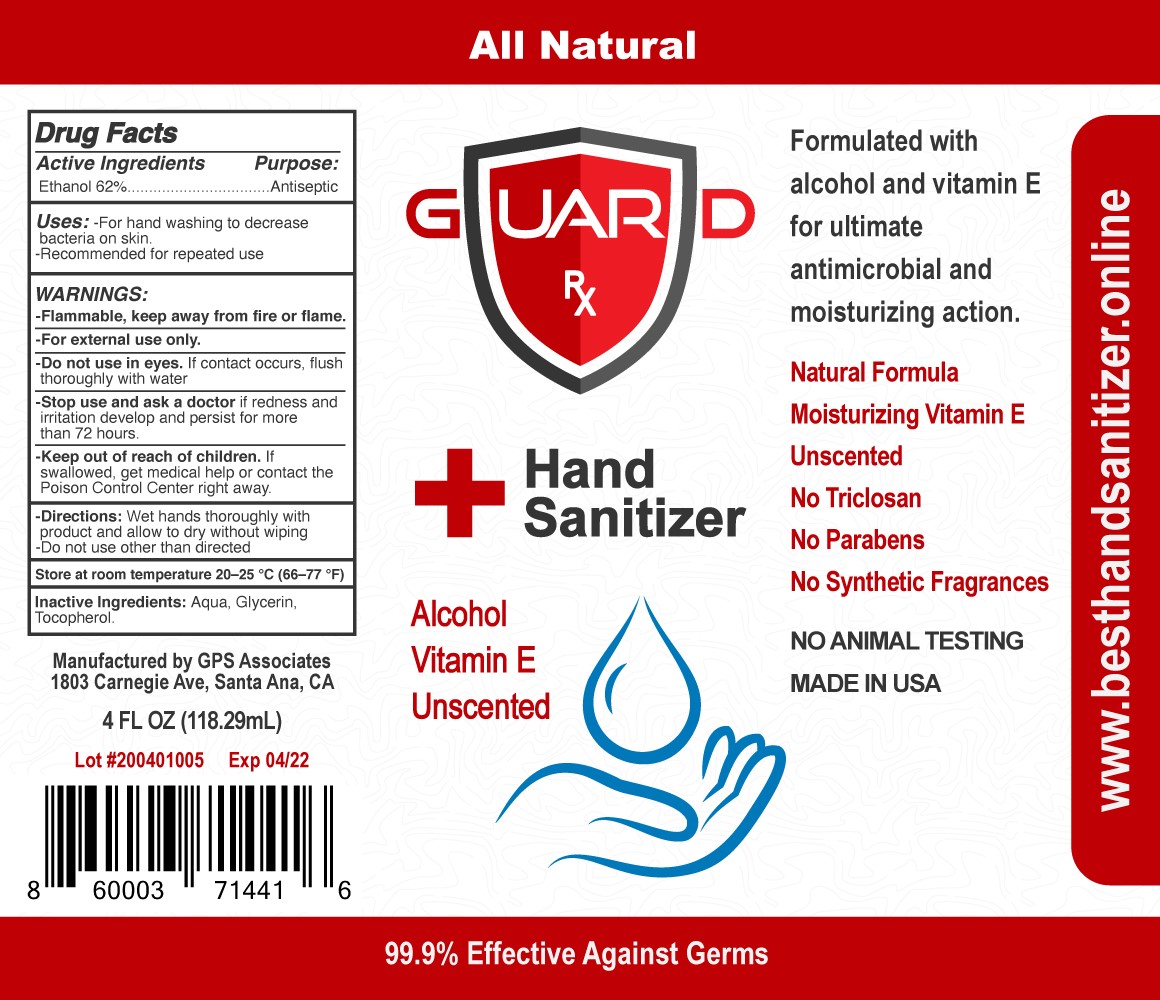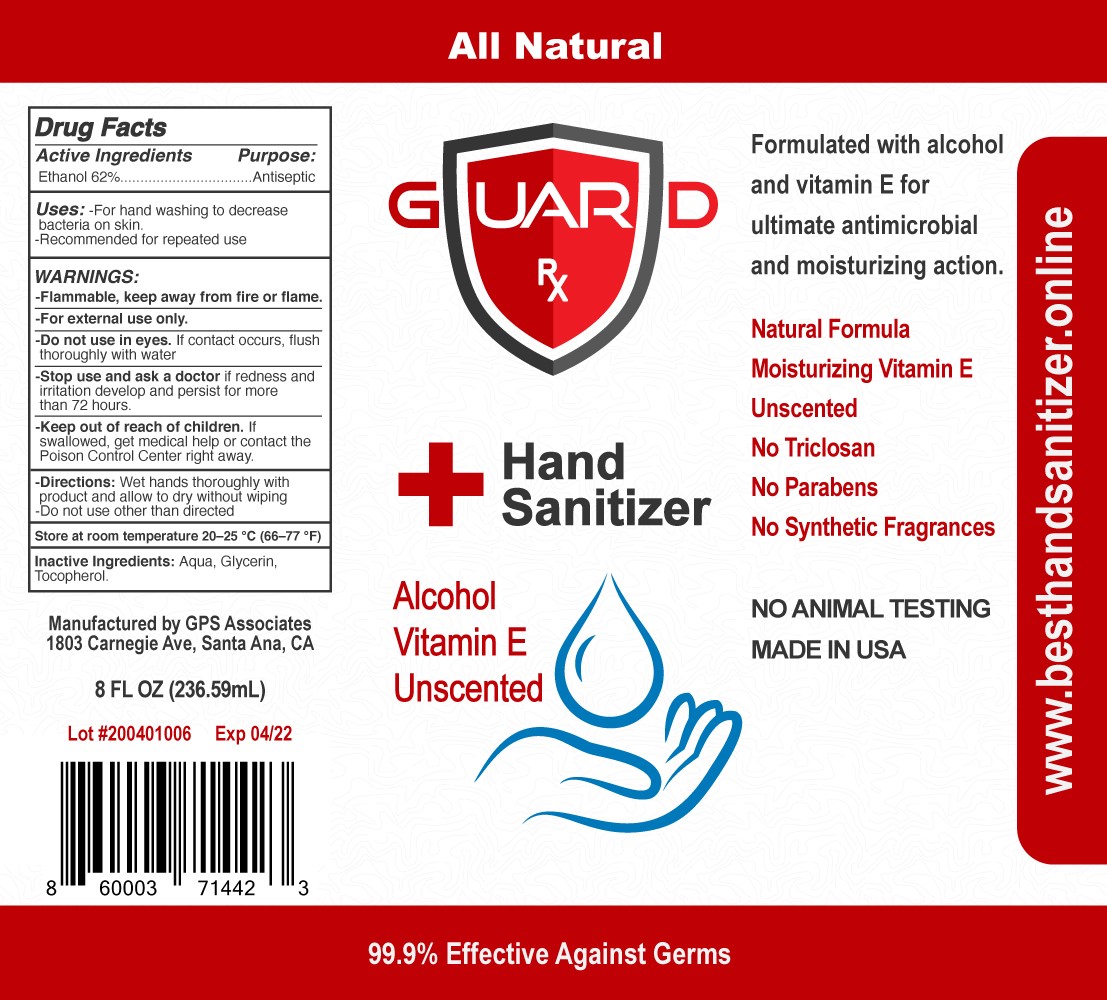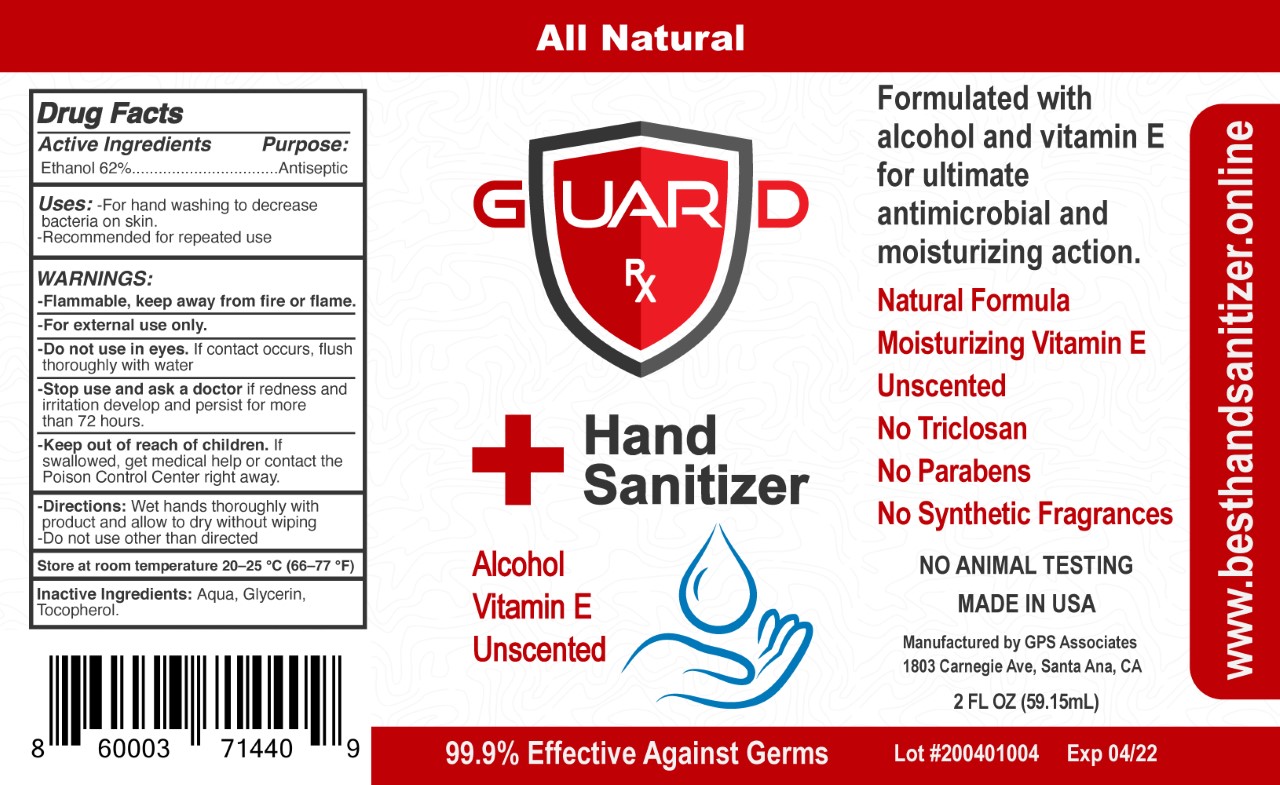 DRUG LABEL: GuardRx Red Thyme
NDC: 74306-123 | Form: LIQUID
Manufacturer: GPS Associates
Category: otc | Type: HUMAN OTC DRUG LABEL
Date: 20200326

ACTIVE INGREDIENTS: ALCOHOL 62 mL/100 mL
INACTIVE INGREDIENTS: ORANGE OIL; WATER; THYME OIL; GLYCERIN; .ALPHA.-TOCOPHEROL, DL-

Guard Rx Hand Sanitizer Red Thyme Oil

Active Ingredients:

Ethanol 62%

Uses:

-For hand washing to decrease bacteria on skin.

-Recommended for repeated use.

WARNINGS:

-Flammable, keep away from children.

WHEN USING

-For external use only.

-Do not use in eyes. If contact occurs, flush thoroughly with water.

-Stop use and ask a doctor if redness and irritation develop and persist for more than 72 hours.

KEEP OUT OF REACH OF CHILDREN

-Keep our of reach of children. If swallowed, get medical help or contact the Poison Control Center right away.

Directions:

Wet hands thoroughly with product and allow to dry without wiping.

-Do not use other than directed.

STORAGE AND HANDLING

Store at room temperature 20-25 °C (66-77 °F)

Inactive Ingredients:

Aqua, Glycerin, Citrus Aurantium Dulcis (Orange) Peel Oil, Thymus Vulgaris (Red Thyme) Oil, Tocopherol.

Active Ingredients:

Ethanol 62%

Purpose:

Antiseptic

Uses:

-For hand washing to decrease bacteria on skin.

-Recommended for repeated use.

WARNINGS:

-Flammable, keep away from children.

WHEN USING

-For external use only.

-Do not use in eyes. If contact occurs, flush thoroughly with water.

-Stop use and ask a doctor if redness and irritation develop and persist for more than 72 hours.

KEEP OUT OF REACH OF CHILDREN

-Keep our of reach of children. If swallowed, get medical help or contact the Poison Control Center right away.

Directions:

Wet hands thoroughly with product and allow to dry without wiping.

-Do not use other than directed.

STORAGE AND HANDLING

Store at room temperature 20-25 °C (66-77 °F)

Inactive Ingredients:

Aqua, Glycerin, Lavandula Angustifolia (Lavender) Oil, Mentha Piperita (Peppermint) Oil, Tocopherol.

Active Ingredients:

Ethanol 62%

Purpose:

Antiseptic

Uses:

-For hand washing to decrease bacteria on skin.

-Recommended for repeated use.

WARNINGS:

-Flammable, keep away from children.

WHEN USING

-For external use only.

-Do not use in eyes. If contact occurs, flush thoroughly with water.

-Stop use and ask a doctor if redness and irritation develop and persist for more than 72 hours.

KEEP OUT OF REACH OF CHILDREN

-Keep our of reach of children. If swallowed, get medical help or contact the Poison Control Center right away.

Directions:

Wet hands thoroughly with product and allow to dry without wiping.

-Do not use other than directed.

STORAGE AND HANDLING

Store at room temperature 20-25 °C (66-77 °F)

Inactive Ingredients:

Aqua, Glycerin, Tocopherol.